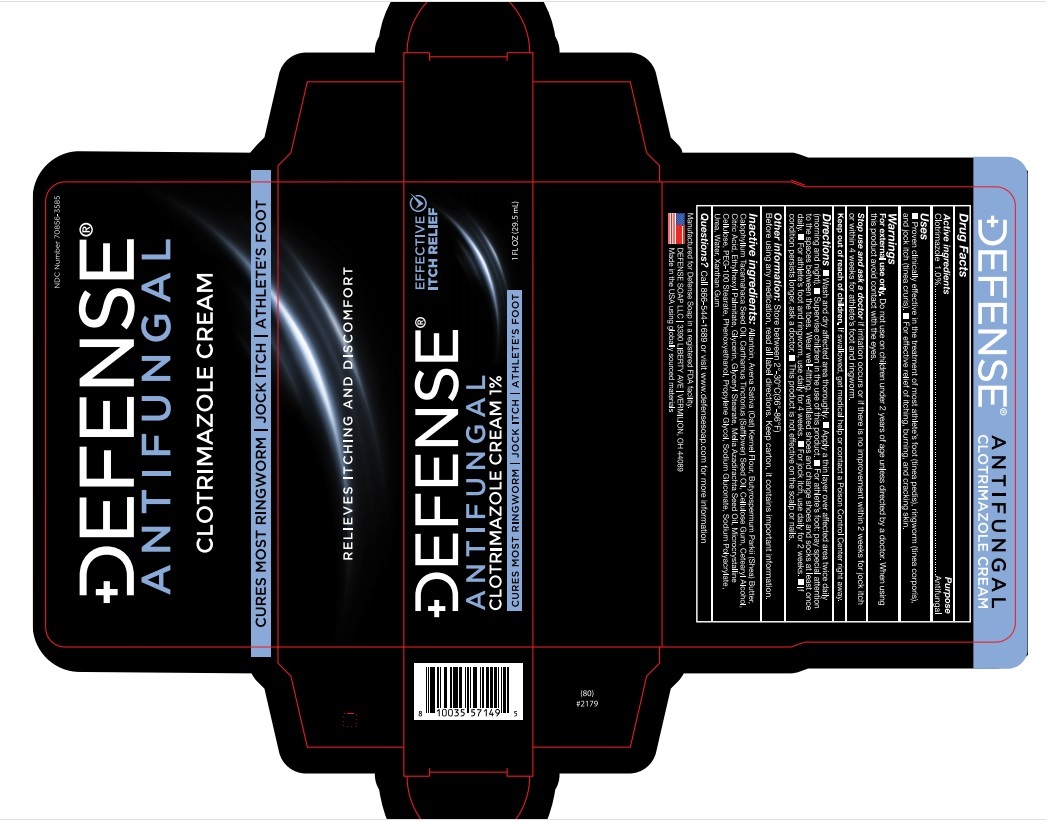 DRUG LABEL: Antifungal 1% Clotrimazole Cream
NDC: 70856-3585 | Form: CREAM
Manufacturer: Defense Soap LLC
Category: otc | Type: HUMAN OTC DRUG LABEL
Date: 20251217

ACTIVE INGREDIENTS: CLOTRIMAZOLE 1 g/100 mL
INACTIVE INGREDIENTS: UREA; GLYCERIN; WATER; CALOPHYLLUM TACAMAHACA SEED OIL; ETHYLHEXYL PALMITATE; PHENOXYETHANOL; CELLULOSE, MICROCRYSTALLINE; ANHYDROUS CITRIC ACID; CARBOXYMETHYLCELLULOSE SODIUM, UNSPECIFIED FORM; AZADIRACHTA INDICA SEED OIL; OATMEAL; SHEA BUTTER; SODIUM GLUCONATE; XANTHAN GUM; GLYCERYL MONOSTEARATE; SAFFLOWER OIL; CETOSTEARYL ALCOHOL; PEG-100 STEARATE; SODIUM POLYACRYLATE (8000 MW); ALLANTOIN; PROPYLENE GLYCOL

Defense 1% Clotrimazole antifungal cream

Inactive Ingredients

Inactive ingredients: Allantoin, Avena Sativa (Oat) Kemel Flour, Butyrospermum Parkii (Shea) Butter,
Calophyllum Tacamahaca Seed Oil, Carthamus Tinctorius (Safflower) Seed Oil, Cellulose Gum, Cetearyl Alcohol,
Citric Acid, Ethylhexyl Palmitate, Glycerin, Glyceryl Stearate. Melia Azadirachta Seed Oil, Microcrystalline
Cellulose, PEG-100 Stearate, Phenoxyethanol, Propylene Glycol, Sodium Gluconate, Sodium Polyacrylate,
Urea, Water, Xanthan Gum

Active Ingredient

Active ingredients: Clotrimazole 1.0%

Purpose

Antifungal

Warnings

Keep out of reach of children. If swallowed, get medical help or contact a Poison Control Center right away.

Directions

Directions Wash and diy affected area thoroughly. Apply a thin layer over affected area twice daily
(moming and night). Supervise children in the use of this product. For athlete’s foot: pay special attention
to the spaces between the toes. Wear well-fitting, ventilated shoes and change shoes and socks at least once
daily. For athlete’s foot and ringworm. use daily for 4 weeks. For jock itch, use daily for 2 weeks. If
condition persists longer, ask a doctor. This product is not effective on the scalp or nails

Uses

Proven clinically effective in the treatment of most athlete's foot (tinea pedis), ringworm (tinea corporis), and jock itch (tinea cruris). For effective relief of itching, burning, and cracking skin.

Warnings

For external use only. Do not use on children under 2 years of age unless directed by a doctor. When using this product avoid contact with eyes.

Stop use and ask a doctor if irritation occurrs or if there is no improvement within 2 weeks for jock itch or within 4 weeks for athlete's foot and ringworm.
Keep out of reach of children. If swallowed, get medical help or contact a Poison Control Center right away.